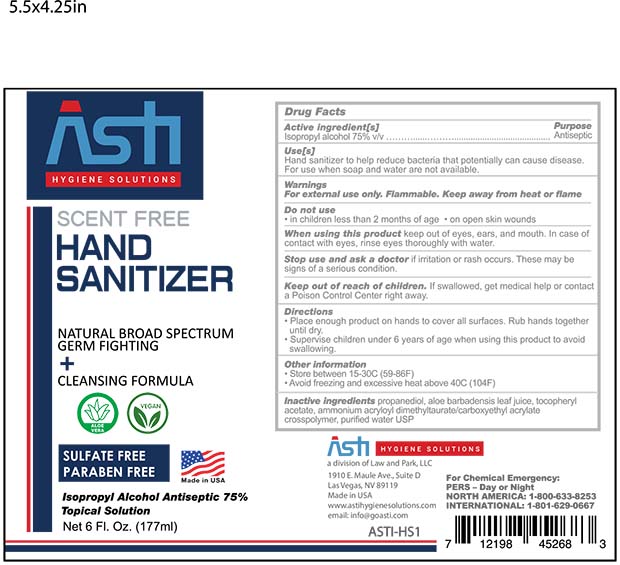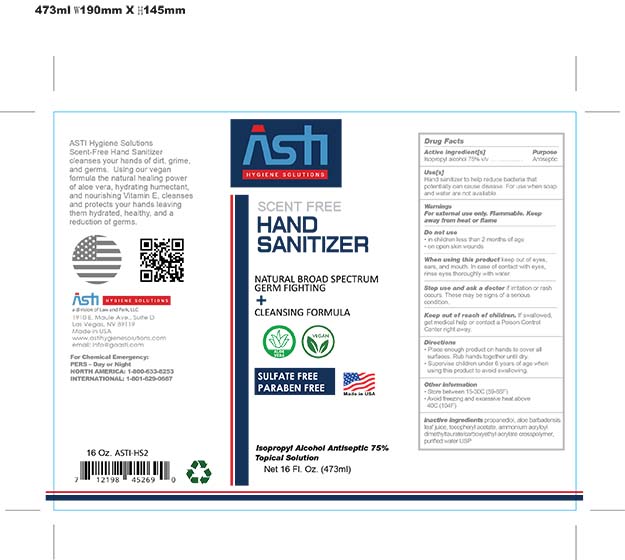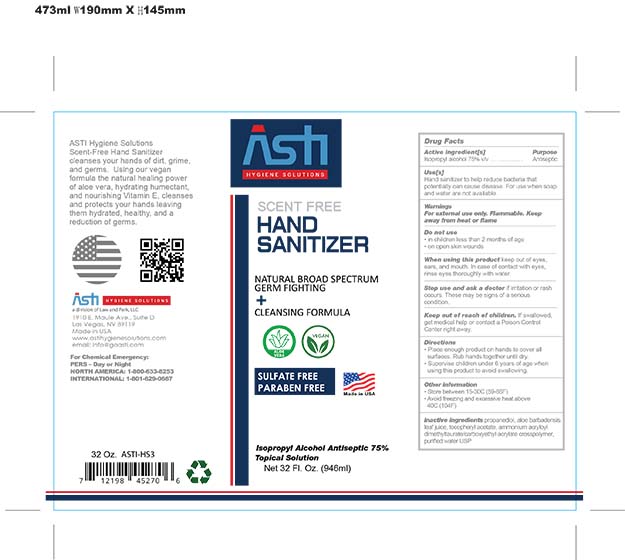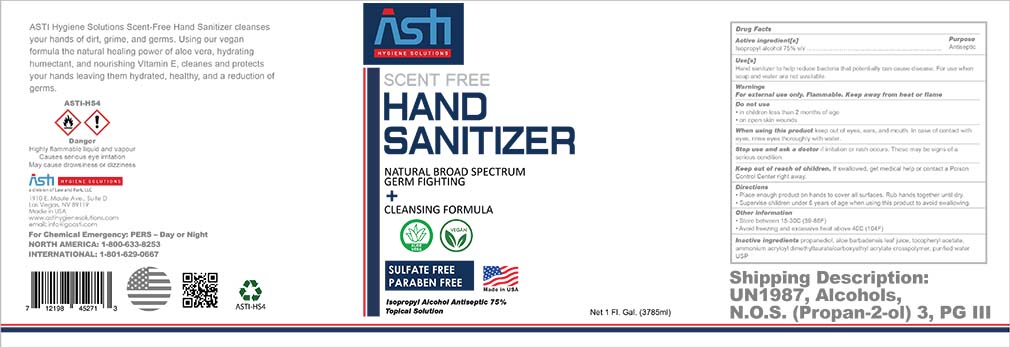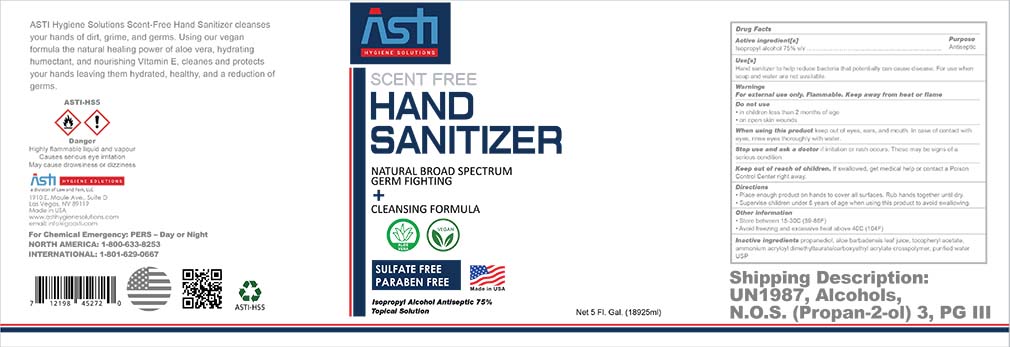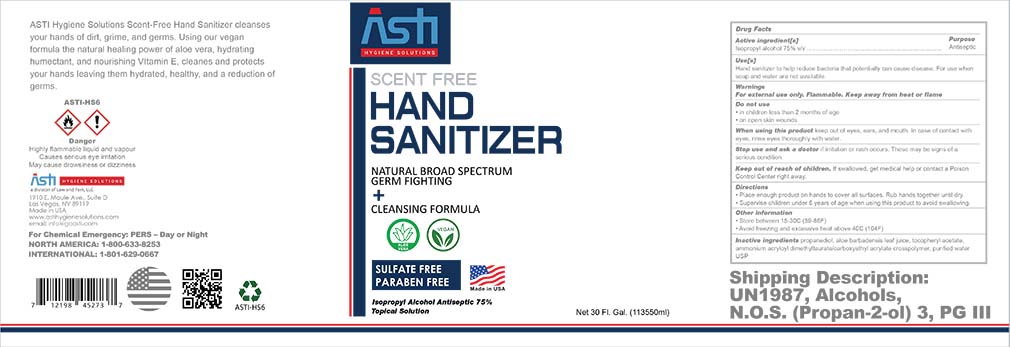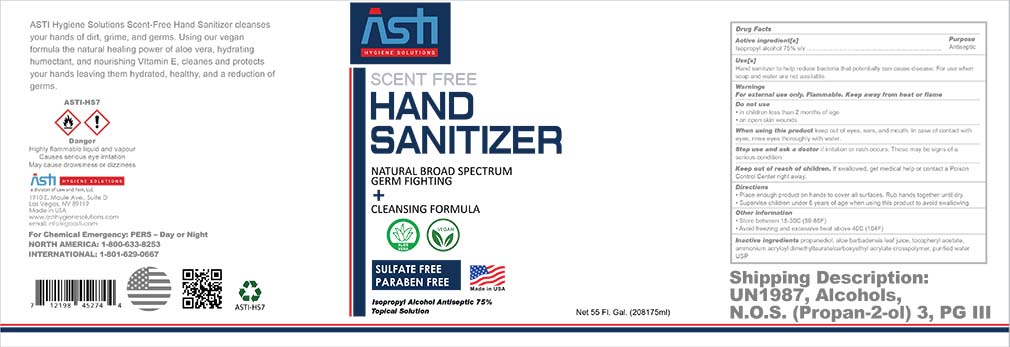 DRUG LABEL: Hand Sanitizer - Asti
NDC: 74624-001 | Form: GEL
Manufacturer: Total Import Solutions, Inc.
Category: otc | Type: HUMAN OTC DRUG LABEL
Date: 20200518

ACTIVE INGREDIENTS: ISOPROPYL ALCOHOL 75 mL/100 mL
INACTIVE INGREDIENTS: ALPHA-TOCOPHEROL ACETATE 0.04 mL/100 mL; PROPANEDIOL 2 mL/100 mL; ALOE VERA LEAF 0.1 mL/100 mL; WATER 21.36 mL/100 mL; AMMONIUM ACRYLOYLDIMETHYLTAURATE 1.5 mL/100 mL

Active Ingredient(s)

Isopropyl Alcohol 75% v/v. Purpose: Antiseptic

Purpose

Antiseptic, Hand Sanitizer

Use

Hand Sanitizer to help reduce bacteria that potentially can cause disease. For use when soap and water are not available.

Warnings

For external use only. Flammable. Keep away from heat or flame

When using this product keep out of eyes, ears, and mouth. In case of contact with eyes, rinse eyes thoroughly with water.
Stop use and ask a doctor if irritation or rash occurs. These may be signs of a serious condition.
Keep out of reach of children. If swallowed, get medical help or contact a Poison Control Center right away.

Stop use and ask a doctor if irritation or rash occurs. These may be signs of a serious condition.

Keep out of reach of children. If swallowed, get medical help or contact a Poison Control Center right away.

Directions

- Place enough product on hands to cover all surfaces. Rub hands together until dry.
- Supervise children under 6 years of age when using this product to avoid swallowing.

Other information

- Store between 15-30C (59-86F)
- Avoid freezing and excessive heat above 40C (104F)

Inactive ingredients

purified water USP, Propanediol, Aloe Barbadensis Leaf Juice, Ammonium Mcryloyl Dimethyltaurate/Carboxyethyl Acrylate Crosspolymer, Tocopheryl Acetate

Package Label - Principal Display Panel

177 ml NDC: 74624-001-01

473 ml NDC: 74624-001-02

946 ml NDC: 74624-001-03

3785 ml NDC: 74624-001-04

18927 ml NDC: 74624-001-05 -

113562 ml NDC: 74624-001-06

208198 ml NDC: 74624-001-07